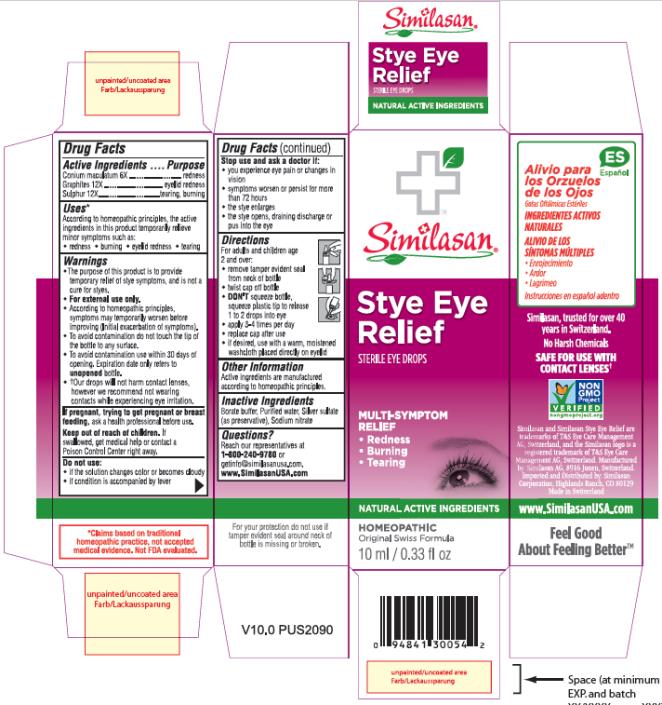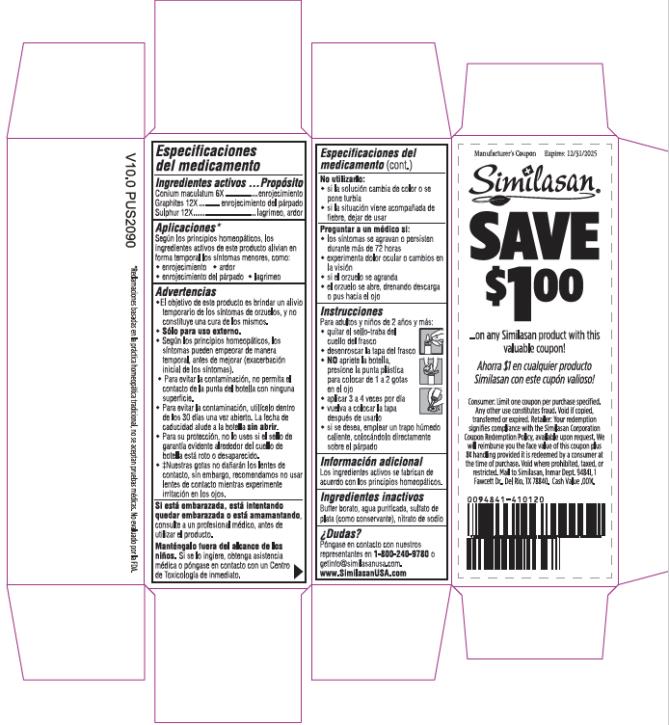 DRUG LABEL: Stye Eye Relief
NDC: 53799-305 | Form: SOLUTION/ DROPS
Manufacturer: Similasan AG
Category: homeopathic | Type: HUMAN OTC DRUG LABEL
Date: 20211007

ACTIVE INGREDIENTS: CONIUM MACULATUM FLOWERING TOP 6 [hp_X]/10 mL; GRAPHITE 12 [hp_X]/10 mL; SULFUR 12 [hp_X]/10 mL
INACTIVE INGREDIENTS: BORIC ACID; WATER; SILVER SULFATE; SODIUM NITRATE

Stye Eye Relief

Active Ingredient

Conium maculatum 6X

Purpose

redness

Active Ingredient

Graphites 12X

Purpose

eyelid redness

Active Ingredient

Sulphur 12X

Purpose

tearing, burning

Uses:

According to homeopathic principles, the active ingredients in this medication temporarily relieve minor symptoms such as:

- redness
- burning
- eyelid redness
- tearing

Warnings:

- The purpose of this product is to provide temporary relief of stye symptoms, and is not a cure for styes.
- For external use only.
- According to homeopathic principles, symptoms may temporarily worsen before improving (Initial exacerbation of symptoms).
- To avoid contamination do not touch the tip of the container to any surface.
- To avoid contamination use within 30 days of opening. Expiration date only refers to unopened bottle.
- †Our drops will not harm contact lenses, however we recommend not wearing contacts while experiencing eye irritation.

If pregnant, trying to get pregnant or breast feeding,

ask a health professional before use.

Keep out of reach of children.

If swallowed, get medical help or contact a Poison Control Center right away.

Do not use:

- if the solution changes color or becomes cloudy
- if condition is accompanied by fever

Stop use and ask a doctor if:

- you experience eye pain or changes in vision
- symptoms worsen or persist for more than 72 hours
- the stye enlarges
- the style opens, draining discharge or pus into the eye

Directions:

For adults and children age 2 and over:

- remove tamper evident seal from neck of bottle
- twist cap off bottle
- DON’T squeeze bottle, squeeze plastic tip to release 1 to 2 drops into eye
- apply 3-4 times per day
- replace cap after use
- if desired, use with a warm, moistened washcloth placed directly on eyelid

Other Information:

Active ingredients are manufactured according to homeopathic principles.

Inactive ingredients:

Borate buffer, Purified water, Silver sulphate (as preservative), Sodium nitrate

Questions?

Reach our representatives at 1-800-240-9780 or getinfo@similasanusa.com.
www.SimilasanUSA.com

PRINCIPAL DISPLAY PANEL

Similasan
Stye Eye Relief
STERILE EYE DROPS
10 ml / 0.33 fl oz